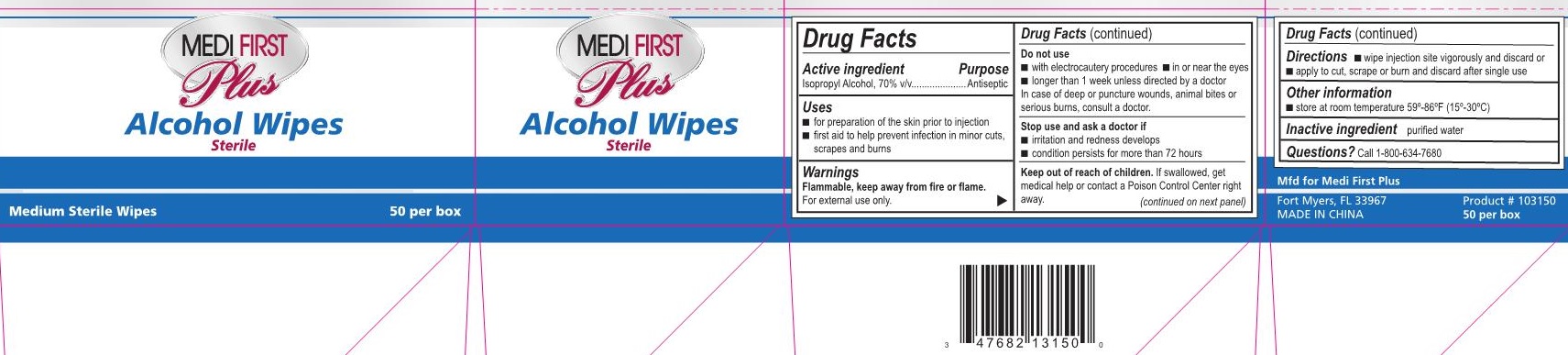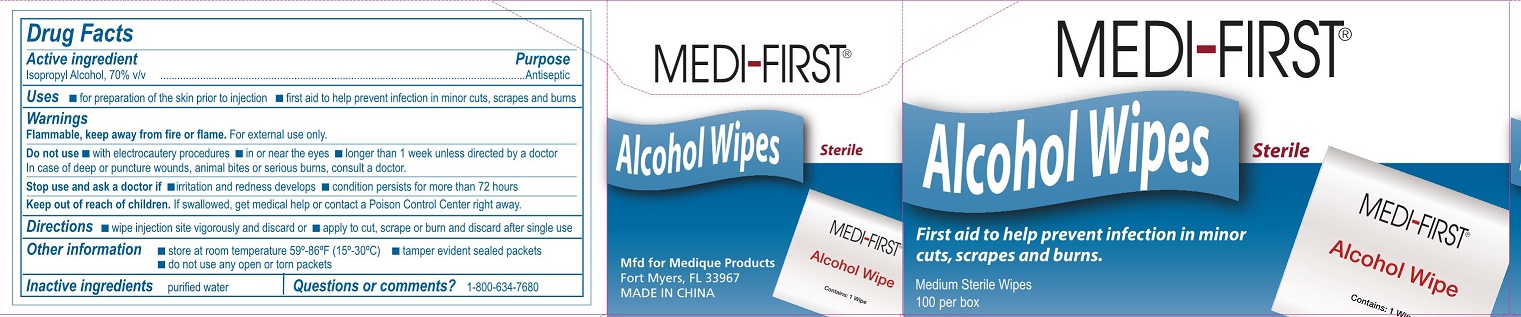 DRUG LABEL: Medi-First Alcohol Wipes
NDC: 47682-222 | Form: SWAB
Manufacturer: Unifirst First Aid Corporation
Category: otc | Type: HUMAN OTC DRUG LABEL
Date: 20250908

ACTIVE INGREDIENTS: ISOPROPYL ALCOHOL 0.7 mL/1 1
INACTIVE INGREDIENTS: WATER

Medi-First Alcohol Wipes

Active ingredient

Isopropyl alcohol, 70% v/v

Purpose

Antiseptic

Uses

- for preparartion of the skin prior to injection
- first aid to help prevent infection in minor cuts, scrapes and burns

Warnings

Flammable, keep away from fire or flame.

For external use only.

Do not use

- with electrocautery procedures
- in or near the eyes
- longer than 1 week unless directed by a doctor

In case of deep or puncture wounds, animal bites or serious burns, consult a doctor.

Stop use and ask a doctor if

- irritation and redness develops
- condition persists for more than 72 hours

Keep out of reach of children.

If swallowed, get medical help or contact a Poison Control Center right away.

Directions

- wipe injection site vigorously and discard or
- apply to cut, scrape or burn and discard after single use

Other information

- store at room temperature 59°-86°F (15°-30°C)
- tamper evidentsealed packets
- do not use any open or torn packets

Inactive ingredient

purified water

Questions or comments?

Call 1-800-634-7680

Medi-First Alcohol Wipes Label

Medi-First®

Alcohol Wipes Sterile

First aid to help prevent infection in minor cuts,scrapes and burns.

Medium Sterile Wipes

100 per box

Medi-First Plus Alcohol Wipes Label

Medi-First Plus®

Alcohol Wipes

Sterile

Medium Sterile Wipes

50 per box